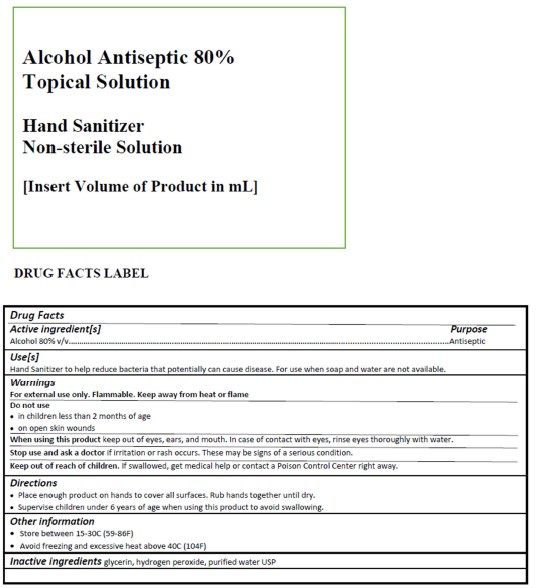 DRUG LABEL: Hand Santizer
NDC: 74054-100 | Form: LIQUID
Manufacturer: Robert Mazza, Inc dba Five & 20 Spirits
Category: otc | Type: HUMAN OTC DRUG LABEL
Date: 20200421

ACTIVE INGREDIENTS: ALCOHOL 80 mL/100 mL
INACTIVE INGREDIENTS: GLYCERIN; HYDROGEN PEROXIDE; WATER

DOSAGE AND ADMINISTRATION

For topical use only

ACTIVE INGREDIENT

Alcohol - 80%ABV

INACTIVE INGREDIENT

Glycerin, Hydrogen Peroxide, Water

INDICATIONS AND USAGE

For external use only

Keep out of reach of children

PURPOSE

Sanitizer - for hands

WARNINGS

For external use only, flammable, keep away from heat or flame.